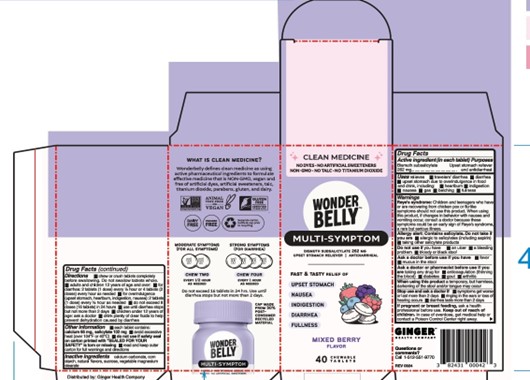 DRUG LABEL: Wonderbelly Multi-Symptom
NDC: 82431-301 | Form: TABLET, CHEWABLE
Manufacturer: Ginger Health Company
Category: otc | Type: HUMAN OTC DRUG LABEL
Date: 20250301

ACTIVE INGREDIENTS: BISMUTH SUBSALICYLATE 262 mg/1 1
INACTIVE INGREDIENTS: CALCIUM CARBONATE; MAGNESIUM STEARATE; STARCH, CORN; SUCROSE

Wild berry Multi Symptom

Drug Facts

Active ingredient (in each tablet)

Bismuth subsalicylate 262 mg

Purposes

Upset stomach reliever and antidiarrheal

Uses

relieves

- travelers' diarrhea
- diarrhea
- upset stomach due to overindulgence in food and drink, including:
- heartburn
- indigestion
- naueas
- gas
- belching
- fullness

Warnings

Reyes Syndrome: Children and teenagers who have or are recovering from chicken pox or flu-like symptoms should not use this product. When using this product, if changes in behavior with nausea and vomitting occur, consult a doctor because these symptoms could be an early sign of Reye's syndrom, a rare but serious illness.

Allergy alert: Contains salicylate. Do not take if you are

- allergic to salicylates (including aspirin)
- taking other salicylate products

Do not use if

you have

- an ulcer
- a bleeding problem
- bloody or black stool

Ask a doctor before use if you have

- fever
- mucus in the stool

Ask a doctor or pharmacist before use if you are

taking any drug for

- anticoagulation (thinning the blood)
- diabetes
- gout
- arthritis

When using this product

a temporary, but harmless, darkening of the stool and/or tongue may occur

Stop use and ask a doctor if

- symptoms get worse or last more than 2 days
- ringing in the ears or loss of hearing occurs
- diarrhea lasts more than 2 days

If pregnant or breast feeding,

ask a health professional before use.

Keep out of reach of children.

In case of overdose, get medical help or contact a Poison Control Center right away.

Directions

- chew or crush tablets completely before swallowing. Do not swallow tablets whole.
- adults and children 12 years of age and over:
- for diarrhea: 2 tablets (1 dose) every 1/2 hour or 4 tablets (2 doses) every hour as needed
- for overindulgence (upset stomach, heartburn, indigestion, nausea): 2 tablets (1 dose) every 1/2 hour as needed
- do not exceed 8 doses (16 tablets) in 24 hours
- use until diarrhea stops but not more than 2 days
- children under 12 years of age: ask a doctor
- drink plenty of clear fluids to help prevent dehydration caused by diarrhea

Other information

- each tablet contains: calcium 65mg, salicylate 102 mg
- avoid excessive heat (over 104°F or 40°C)
- do not use if safety seal on carton printed with "SEALED FOR YOUR SAFETY" is torn or missing
- read and keep outer carton for full warnings and directions

Inactive ingredients

calcium carbonate, corn starch, natural flavors, sucrose, vegetable magnesium stearate

Questions or comments?

call 1-512-551-9770

Distributed by:

Ginger Health Company

Austin, Texas 78702

Principal Display Panel

CLEAN MEDICINE

No Dyes, No Artificial Sweeteners, Non-GMO, No Talc, No Titanium Dioxide

WONDERBELLY

MULTI-SYMPTOM

Bismuth Subsalicylate 262 mg

Upset Stomach Reliever | Antidiarrheal

Fast & Tasty Relief of

Upset Stomach

Nausea

Indigestion

Diarrhea

Fullness

MIXED BERRY

Flavor

40 Chewable Tablets